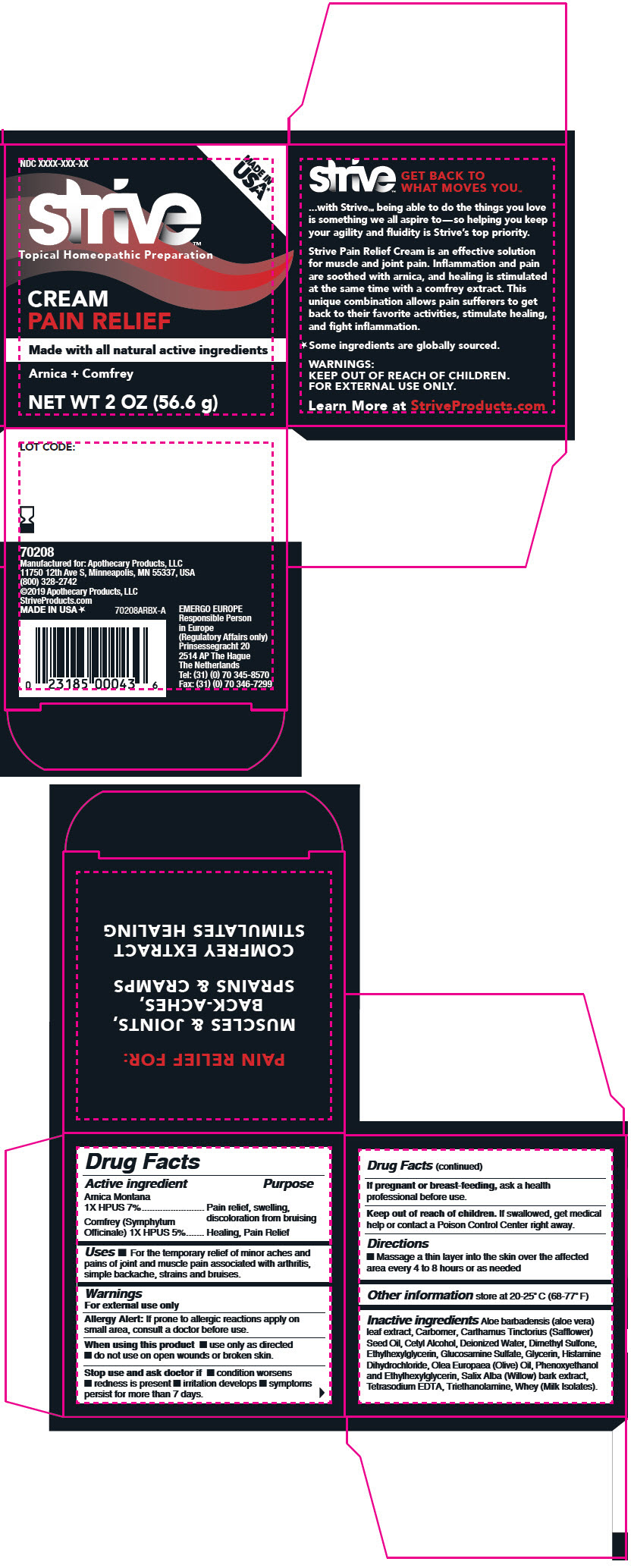 DRUG LABEL: Strive Pain Relief
NDC: 63374-002 | Form: CREAM
Manufacturer: Steuart Custom Manufacturing
Category: homeopathic | Type: HUMAN OTC DRUG LABEL
Date: 20190403

ACTIVE INGREDIENTS: Arnica Montana Flower 1 [hp_X]/1 g; Comfrey Leaf 1 [hp_X]/1 g
INACTIVE INGREDIENTS: Aloe Vera Leaf; Cetyl Alcohol; Glycerin; Safflower oil; Ethylhexylglycerin; Phenoxyethanol; Methylparaben; Propylparaben; Salix Alba Bark; Dimethyl Sulfone; GLUCOSAMINE SULFATE POTASSIUM CHLORIDE; Water; Histamine Dihydrochloride; Carbomer Copolymer Type B (Allyl Pentaerythritol Crosslinked); Trolamine; Whey

Strive™ Pain Relief Cream

Drug Facts

ACTIVE INGREDIENT

Active ingredient |  | Purpose
Arnica Montana 1X HPUS 7% | Pain relief, swelling, discoloration from bruising
Comfrey (Symphytum Officinale) 1X HPUS 5% | Healing, Pain Relief

Uses

- For the temporary relief of minor aches and pains of joint and muscle pain associated with arthritis, simple backache, strains and bruises.

Warnings

For external use only

Allergy Alert

If prone to allergic reactions apply on small area, consult a doctor before use.

When using this product

- use only as directed
- do not use on open wounds or broken skin.

Stop use and ask doctor if

- condition worsens
- redness is present
- irritation develops
- symptoms persist for more than 7 days.

PREGNANCY OR BREAST FEEDING

If pregnant or breast-feeding, ask a health professional before use.

Keep out of reach of children. If swallowed, get medical help or contact a Poison Control Center right away.

Directions

- Massage a thin layer into the skin over the affected area every 4 to 8 hours or as needed

Other information

store at 20-25° C (68-77° F)

Inactive ingredients

Aloe barbadensis (aloe vera) leaf extract, Carbomer, Carthamus Tinctorius (Safflower) Seed Oil, Cetyl Alcohol, Deionized Water, Dimethyl Sulfone, Ethylhexylglycerin, Glucosamine Sulfate, Glycerin, Histamine Dihydrochloride, Olea Europaea (Olive) Oil, Phenoxyethanol and Ethylhexylglycerin, Salix Alba (Willow) bark extract, Tetrasodium EDTA, Triethanolamine, Whey (Milk Isolates).

PRINCIPAL DISPLAY PANEL - 56.6 g Jar Carton

NDC XXXX-XXX-XX

MADE IN
USA

strive™
Topical Homeopathic Preparation

CREAM
PAIN RELIEF

Made with all natural active ingredients

Arnica + Comfrey

NET WT 2 OZ (56.6 g)